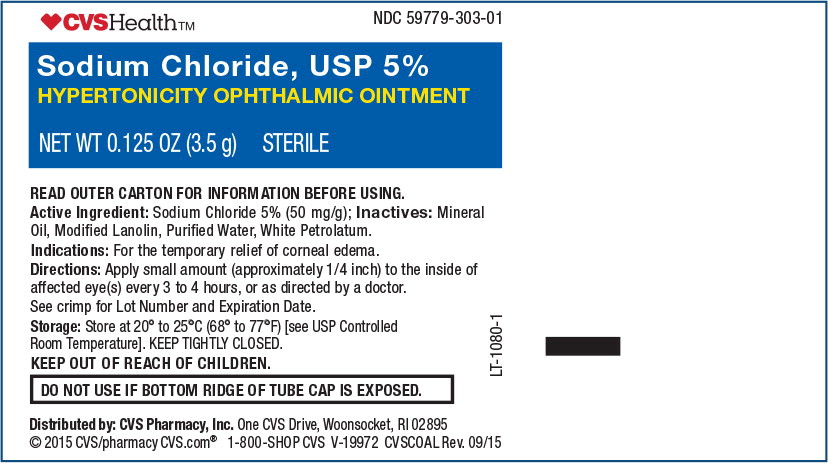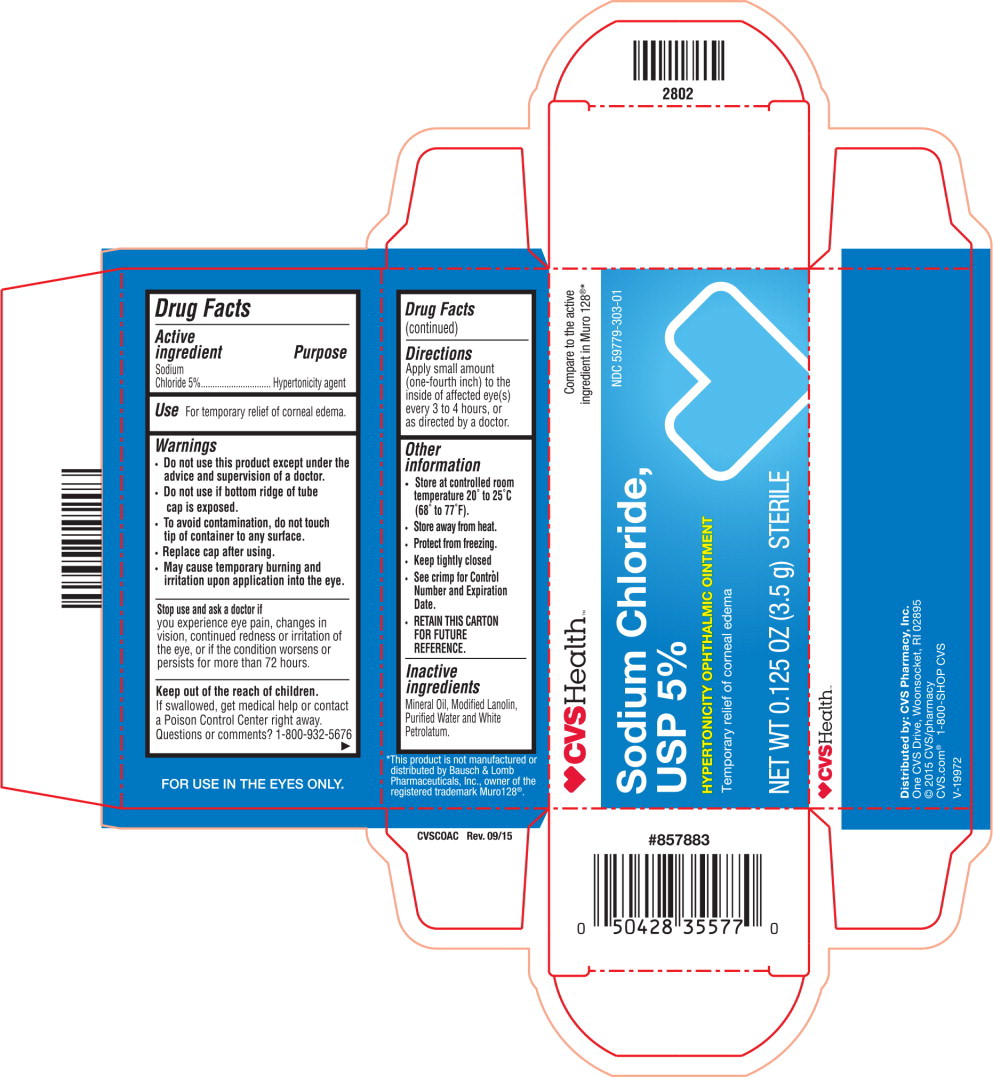 DRUG LABEL: Sodium Chloride
NDC: 59779-303 | Form: OINTMENT
Manufacturer: CVS Pharmacy
Category: otc | Type: HUMAN OTC DRUG LABEL
Date: 20220125

ACTIVE INGREDIENTS: Sodium Chloride 50 mg/1 g
INACTIVE INGREDIENTS: Mineral Oil; Lanolin; Water; Petrolatum

Drug Facts

Active ingredient

Sodium Chloride 5%

Purpose

Hypertonicity agent

Use

For temporary relief of corneal edema.

Warnings

- Do not use this product except under the advice and supervision of a doctor.
- Do not use if bottom ridge of tube cap is exposed.
- To avoid contamination, do not touch tip of container to any surface.
- Replace cap after using.
- May cause temporary burning and irritation upon application into the eye.

Stop use and ask a doctor if

you experience eye pain, changes in vision, continued redness or irritation of the eye, or if the condition worsens or persists for more than 72 hours.

Keep out of the reach of children.

If swallowed, get medical help or contact a Poison Control Center right away.

Directions

Apply small amount (one-fourth inch) to the inside of affected eye(s) every 3 to 4 hours, or as directed by a doctor.

Other information

- Store at controlled room temperature 20° to 25°C (68° to 77°F).
- Store away from heat.
- Protect from freezing.
- Keep tightly closed.
- See crimp for Control Number and Expiration Date.
- RETAIN THIS CARTON FOR FUTURE REFERENCE.

Inactive ingredients

Mineral Oil, Modified Lanolin, Purified Water and White Petrolatum.

Principal Display Panel Text for Container Label:

CVS Health™ Logo NDC 59779-303-01

Sodium Chloride USP, 5%

HYPERTONICITY OPHTHALMIC OINTMENT

NET WT 0.125 OZ (3.5 g) STERILE

Principal Display Panel Text for Carton Label:

CVS Health™ Logo Compare to the active

ingredient in Muro® 128*

Sodium Chloride, NDC 59779-303-01

USP, 5%

HYPERTONICITY OPHTHALMIC OINTMENT

Temporary relief of corneal edema

NET WT 0.125 OZ (3.5 g) STERILE